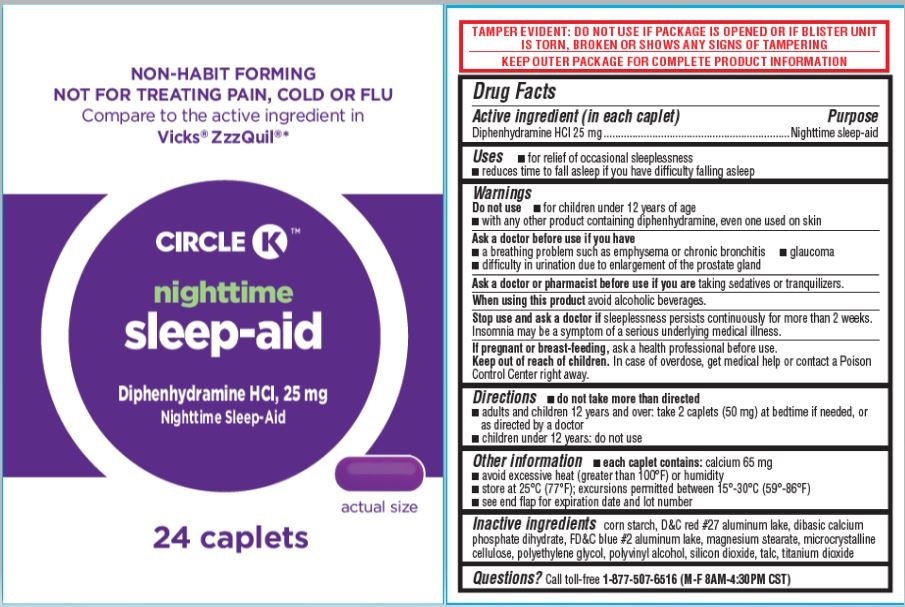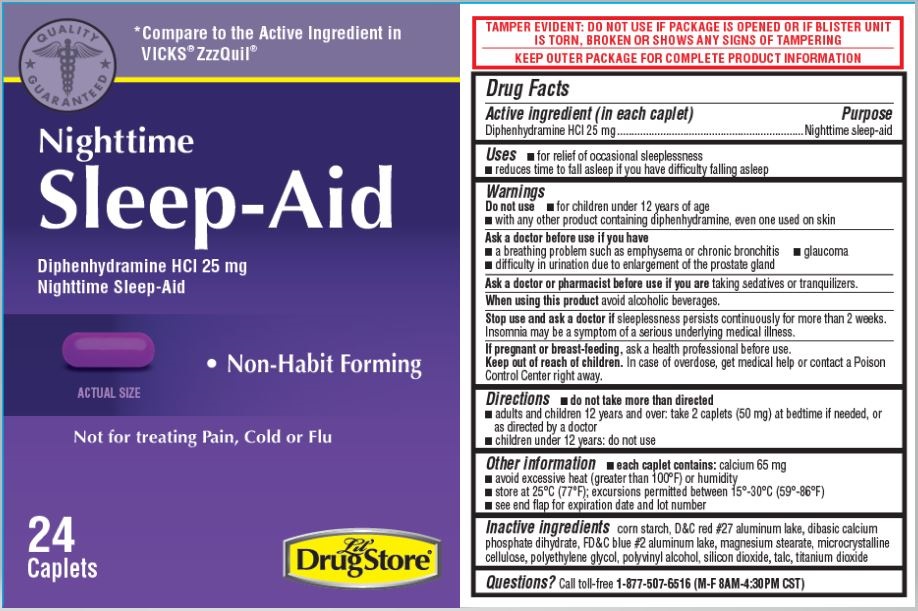 DRUG LABEL: Sleep-Aid, Lil Drug Store
NDC: 66715-6643 | Form: TABLET, FILM COATED
Manufacturer: Lil' Drug Store Products, Inc.
Category: otc | Type: HUMAN OTC DRUG LABEL
Date: 20231214

ACTIVE INGREDIENTS: DIPHENHYDRAMINE HYDROCHLORIDE 25 mg/1 1
INACTIVE INGREDIENTS: POLYETHYLENE GLYCOL, UNSPECIFIED; TALC; TITANIUM DIOXIDE; FD&C BLUE NO. 2--ALUMINUM LAKE; STARCH, CORN; D&C RED NO. 27 ALUMINUM LAKE; DIBASIC CALCIUM PHOSPHATE DIHYDRATE; SILICON DIOXIDE; CELLULOSE, MICROCRYSTALLINE; POLYVINYL ALCOHOL, UNSPECIFIED; MAGNESIUM STEARATE

Sleep-Aid

Active ingredient

Active ingredient (in each caplet)

Diphenhydramine HCl 25 mg

Purpose

Nighttime sleep-aid

Uses

- for relief of occasional sleeplessness
- reduces time to fall asleep if you have difficulty falling asleep

Warnings

Do not use

- for children under 12 years of age
- with any other product containing diphenhydramine, even one used on skin

Ask a doctor before use if you have

- a breathing problem such as emphysema or chronic bronchitis
- glaucoma
- difficulty in urination due to enlargement of the prostate gland

Ask a doctor or pharmacist before use if you are taking sedatives or tranquilizers.

When using this product avoid alcoholic beverages.

Stop use and ask a doctor if sleeplessness persists continuously for more than 2 weeks.
Insomnia may be a symptom of a serious underlying medical illness.

PREGNANCY OR BREAST FEEDING

If pregnant or breast-feeding, ask a health professional before use.

Keep out of reach of children. In case of overdose, get medical help or contact a Poison
Control Center right away.

Directions

- do not take more than directed
- adults and children 12 years and over: take 2 caplets (50 mg) at bedtime if needed, or as directed by a doctor
- children under 12 years: do not use

Other information

- each caplet contains: calcium 65 mg
- avoid excessive heat (greater than 100°F) or humidity
- store at 25°C (77°F); excursions permitted between 15°-30°C (59°-86°F)
- see end flap for expiration date and lot number

Inactive ingredients

corn starch, D&C red #27 aluminum lake, dibasic calcium
phosphate dihydrate, FD&C blue #2 aluminum lake, magnesium stearate, microcrystalline
cellulose, polyethylene glycol, polyvinyl alcohol, silicon dioxide, talc, titanium dioxide

Questions?

Questions? Call toll-free 1-877-507-6516 (M-F 8AM-4:30PM CST)

PDP [Lil' Drug Store Nighttime Sleep-Aid, 24ct]

[caduceus]

*Compare to the Active Ingredient in
VICKS® ZzzQuil®

Nighttime

Sleep-Aid
Diphenhydramine HCI 25 mg
Nighttime Sleep-Aid

[caplet image]

ACTUAL SIZE

- Non-Habit Forming

Not for treating Pain, Cold or Flu
24
Caplets [Lil' Drug Store logo]

PDP [Circle K Nighttime Sleep-Aid, 24ct]

NON-HABIT FORMING
NOT FOR TREATING PAIN, COLD OR FLU
Compare to the active ingredient in
Vicks® ZzzQuil®*

CIRCLE K™

nighttime
sleep-aid
Diphenhydramine HCI, 25 mg
Nighttime Sleep-Aid

[caplet image]

actual size

24 caplets